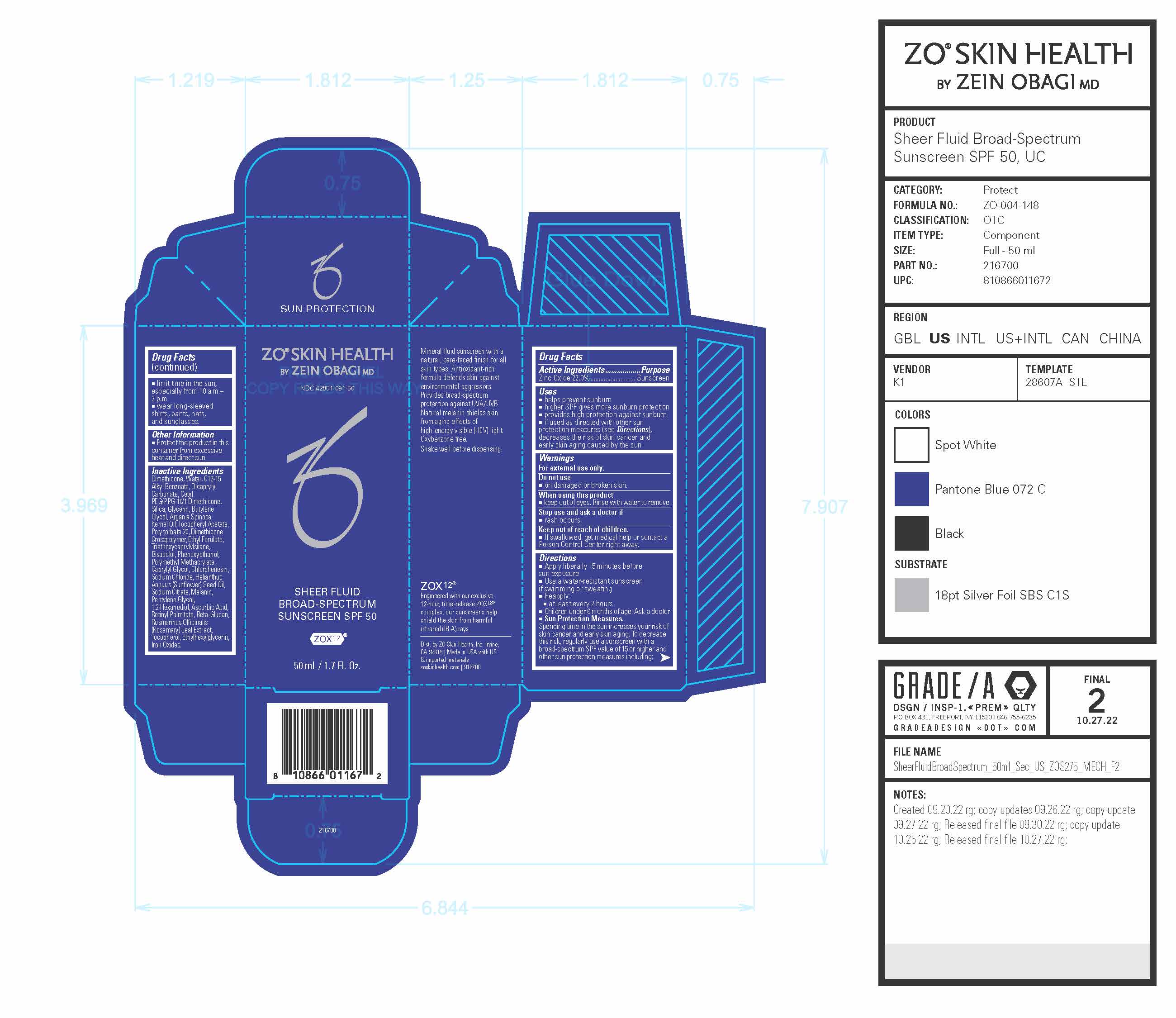 DRUG LABEL: ZO Skin Health Sheer Fluid Broad-Spectrum Sunscreen SPF 50
NDC: 42851-091 | Form: LOTION
Manufacturer: ZO Skin Health, Inc.
Category: otc | Type: HUMAN OTC DRUG LABEL
Date: 20241031

ACTIVE INGREDIENTS: ZINC OXIDE 0.225 g/50 mL
INACTIVE INGREDIENTS: ETHYL FERULATE; SODIUM CHLORIDE; SODIUM CITRATE; MELANIN SYNTHETIC (TYROSINE, PEROXIDE); PENTYLENE GLYCOL; VITAMIN A PALMITATE; TOCOPHEROL; SILICON DIOXIDE; GLYCERIN; ARGAN OIL; ALPHA-TOCOPHEROL ACETATE; POLYSORBATE 20; TRIETHOXYCAPRYLYLSILANE; POLY(METHYL METHACRYLATE; 450000 MW); CAPRYLYL GLYCOL; CHLORPHENESIN; SUNFLOWER OIL; ASCORBIC ACID; WATER; CETYL PEG/PPG-10/1 DIMETHICONE (HLB 4); LEVOMENOL; PHENOXYETHANOL; ROSEMARY; ETHYLHEXYLGLYCERIN; DIMETHICONE; 1,2-HEXANEDIOL; FERRIC OXIDE RED; ALKYL (C12-15) BENZOATE; BUTYLENE GLYCOL; DICAPRYLYL CARBONATE; DIMETHICONE CROSSPOLYMER (450000 MPA.S AT 12% IN CYCLOPENTASILOXANE)

ZO® Skin Health Sheer Fluid Broad-Spectrum Sunscreen SPF 50
National Drug Code 42851-091-50

Drug Facts

Active Ingredients

Active Ingredients | Purpose
Zinc Oxide 22.0% | Sunscreen

Uses

■ helps prevent sunburn
■ higher SPF gives more sunburn protection
■ provides high protection against sunburn
■ if used as directed with other sun protection measures (see Directions), decreases the risk of skin cancer and early skin aging caused by the sun

Warnings

For external use only.

Do not use

- on damaged or broken skin.

When using this product

- keep out of eyes. Rinse with water to remove.

Stop use and ask a doctor if

- rash occurs.

Keep out of reach of children.

- If swallowed, get medical help or contact a Poison Control Center right away.

Directions

- Apply liberally 15 minutes before sun exposure.
- Use a water-resistant sunscreen if swimming or sweating
  - Reapply: ■ at least every 2 hours ■ Children under 6 months of age: Ask a doctor
- Sun Protection Measures. Spending time in the sun increases your risk of skin cancer and early skin aging. To decrease this risk, regularly use a sunscreen with a broad-spectrum SPF value of 15 or higher and other sun protection measures including: ■ limit time in the sun, especially from 10 a.m.–2 p.m. ■ wear long-sleeved shirts, pants, hats, and sunglasses.

Other Information

- Protect the product in this container from excessive heat and direct sun.

Inactive Ingredients

Dimethicone, Water, C12-15 Alkyl Benzoate, Dicaprylyl Carbonate, Cetyl PEG/PPG-10/1 Dimethicone, Silica, Glycerin, Butylene Glycol, Argania Spinosa Kernel Oil, Tocopheryl Acetate, Polysorbate 20, Dimethicone Crosspolymer, Ethyl Ferulate, Triethoxycaprylylsilane, Bisabolol, Phenoxyethanol, Polymethyl Methacrylate, Caprylyl Glycol, Chlorphenesin, Sodium Chloride, Helianthus Annuus (Sunflower) Seed Oil, Sodium Citrate, Melanin, Pentylene Glycol, 1,2-Hexanediol, Ascorbic Acid, Retinyl Palmitate, Beta-Glucan, Rosmarinus Officinalis (Rosemary) Leaf Extract, Tocopherol, Ethylhexylglycerin, Iron Oxides.

Principal Display Panel

ZO® Skin Health

by Zein Obagi MD

NDC 42851-091-50

Sheer Fluid Broad-Spectrum Sunscreen SPF 50

ZOX12®

50 mL / 1.7 Fl. Oz.

Mineral fluid sunscreen with a natural, bare-faced finish for all skin types. Antioxidant-rich formula defends skin against environmental aggressors. Provides broad-spectrum protection against UVA/UVB. Natural melanin shields skin from aging effects of high-energy visible (HEV) light.

Oxybenzone free.

Shake well before dispensing.

ZOX12®

12-hour, time-release ZOX12® complex, our sunscreens help shield the skin from harmful infrared (IR-A) rays.

Dist. by ZO Skin Health, Inc. Irvine, CA 92618 | Made in USA with US & imported materials zoskinhealth.com | 916700